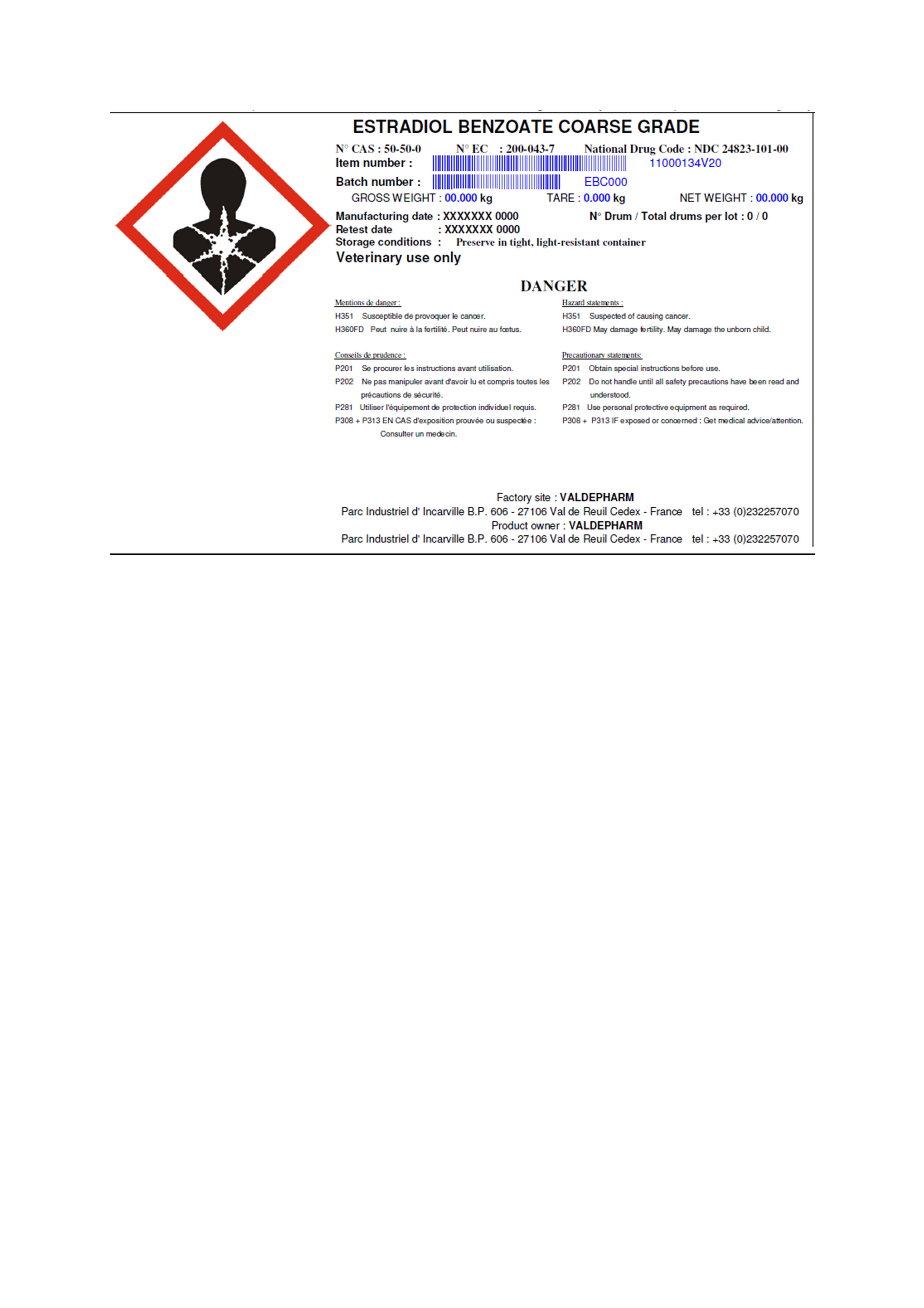 DRUG LABEL: Estradiol Benzoate Coarse Grade
NDC: 24823-101 | Form: POWDER
Manufacturer: Valdepharm
Category: other | Type: BULK INGREDIENT
Date: 20200428

ACTIVE INGREDIENTS: ESTRADIOL BENZOATE 1 kg/1 kg

Estradiol Benzoate Coarse Grade
Registration of label for Pharmaceutical Ingredient